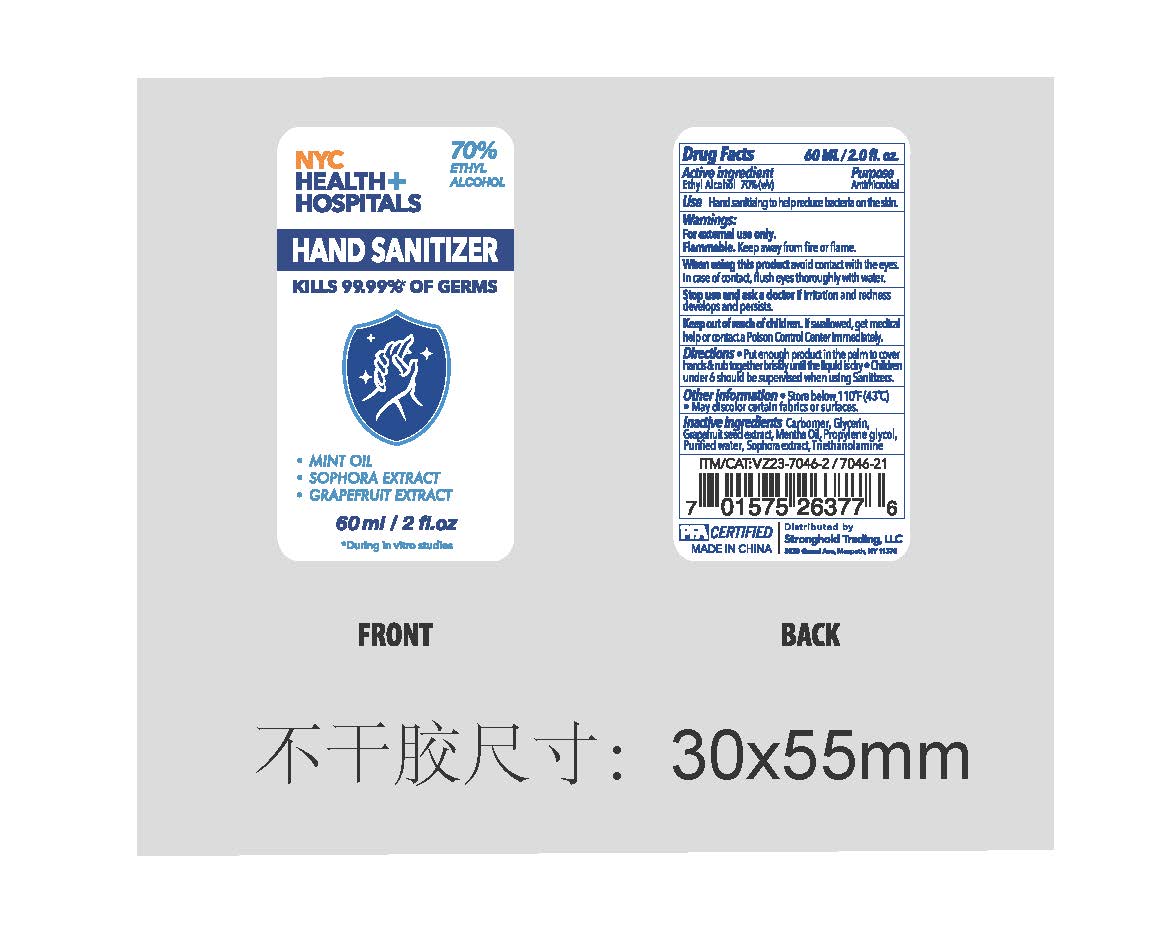 DRUG LABEL: PFA
NDC: 75742-008 | Form: GEL
Manufacturer: Zhejiang Guoyao Jingyue Aerosol Co., Ltd.
Category: otc | Type: HUMAN OTC DRUG LABEL
Date: 20260105

ACTIVE INGREDIENTS: ALCOHOL 70 mL/100 mL
INACTIVE INGREDIENTS: CITRUS PARADISI SEED; MENTHA ARVENSIS LEAF OIL; TROLAMINE; GLYCERIN; WATER; CARBOMER HOMOPOLYMER, UNSPECIFIED TYPE; PROPYLENE GLYCOL; SOPHORA FLAVESCENS ROOT

NYC Health Hospitals Hand Sanitizer

Active Ingredient

Ethyl Alcohol 70% v/v.

Purpose

Antimicrobial

Use

Hand sanitizing to help reduce bacteria on the skin.

Warnings

For external use only. Flammable. Keep away from fire or flame

When using this product avoid contact with the eyes. In case of contact, flush eyes thoroughly with water.

Stop use and ask a doctor if irritation and redness develops or persists.

Keep out of reach of children. If swallowed, get medical help or contact a Poison Control Center immediately.

Directions

- Place enough product on hands to cover hands & rub together briskly until the liquid is dry.
- Children under 6 should be supervised when using Sanitizers.

Other information

- Store below 110F (43C)
- May discolor certain fabrics or surfaces.

Inactive ingredients

Carbomer, Glycerin, Grapefruit seed extract, Mentha Oil, Propylene Glycol, Purified water, Sophora extract, Triethanolamine

Package Label - Principal Display Panel

60 mL/2 fl.oz